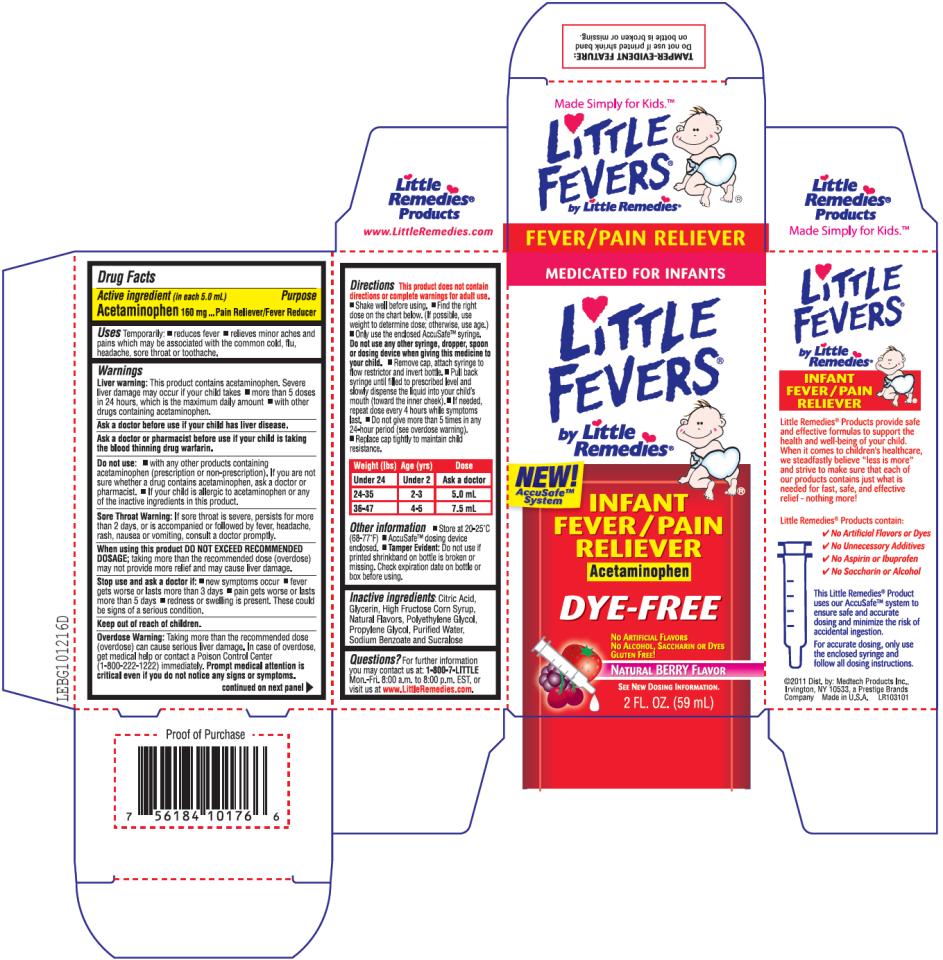 DRUG LABEL: Little Fevers Infant Berry Fever/Pain Reliever
NDC: 63029-622 | Form: LIQUID
Manufacturer: Medtech Products Inc.
Category: otc | Type: HUMAN OTC DRUG LABEL
Date: 20110702

ACTIVE INGREDIENTS: ACETAMINOPHEN 160 mg/5 mL
INACTIVE INGREDIENTS: CITRIC ACID; GLYCERIN; HIGH FRUCTOSE CORN SYRUP; POLYETHYLENE GLYCOL; PROPYLENE GLYCOL; WATER; SODIUM BENZOATE; SUCRALOSE

Little Fevers Infant Berry Fever Pain Reliever

Drug Facts

Active ingredient

(in each 5.0 mL)

Acetaminophen 160mg

Purpose

Pain Reliever/Fever Reducer

Uses

Temporarily:

- reduces fever
- relieves minor aches and pains which may be associated with the common cold, flu, headache, sore throat or toothache.

Warnings

Liver warning: This product contains acetaminophen. Severe liver damage may occur if your child takes

- more than 5 doses in 24 hours, which is the maximum daily amount
- with other drugs containing acetaminophen.

Ask a doctor before use

if your child has liver disease.

Ask a doctor or pharmacist before use

if your child is taking the blood thinning drug warfarin.

Do not use:

- with any other products containing acetaminophen (prescription or non-prescription). If you are not sure whether a drug contains acetaminophen, ask a doctor or pharmacist.
- If your child is allergic to acetaminophen or any of the inactive ingredients in this product.

Sore Throat Warning: If sore throat is severe, persists for more than 2 days, or is accompanied or followed by fever, headache, rash, nausea or vomiting, consult a doctor promptly.

When using this product

DO NOT EXCEED RECOMMENDED DOSAGE; taking more than the recommended dose (overdose) may not provide more relief and may cause liver damage.

Stop use and ask a doctor if:

- new symptoms occur
- fever gets worse or lasts more than 3 days
- pain gets worse or lasts more than 5 days
- redness or swelling is present. These could be signs of a serious condition.

Overdose

Warning: Taking more than the recommended dose (overdose) can cause serious liver damage. In case of overdose, get medical help or contact a Poison Control Center (1-800-222-1222) immediately. Prompt medical attention is critical even if you do not notice any signs or symptoms.

Directions

This product does not contain directions or complete warnings for adult use.

- Shake well before using.
- Find the right dose on the chart below. (If possible, use weight to determine dose; otherwise, use age.)
- Only use the enclosed AccuSafeTM syringe.
- Do not use any other syringe, dropper, spoon or dosing device when giving this medicine to your child.
- Remove cap, attach syringe to flow restrictor and invert bottle.
- Pull back syringe until filled to prescribed level and slowly dispense the liquid into your child’s mouth (toward the inner cheek).
- If needed, repeat dose every 4 hours while symptoms last.
- Do not give more than 5 times in any 24-hour period (see overdose warning).
- Replace cap tightly to maintain child resistance.

Weight (lbs) | Age (yrs) | Dose
Under 24 | Under 2 | Ask a doctor
24-35 | 2-3 | 5.0 mL
36-47 | 4-5 | 7.5 mL

Other information

- Store at 20-25ºC (68-77ºF)
- AccuSafeTM dosing device enclosed.
- Tamper Evident: Do not use if printed shrinkband on bottle is broken or missing. Check expiration date on bottle or box before using.

Inactive ingredients

Citric Acid, Glycerin, High Fructose Corn Syrup, Natural Flavors, Polyethylene Glycol, Propylene Glycol, Purified Water, Sodium Benzoate and Sucralose

Questions?

For further information you may contact us at: 1-800-7-LITTLE Mon. – Fri. 8:00 a.m.to 8:00 p.m. EST, or visit us at www.LittleRemedies.com.

PRINCIPAL DISPLAY PANEL

MEDICATED FOR INFANTS
Little Fevers® by Little Remedies®
NEW! AccuSafeTM System
INFANT FEVER/PAIN RELIEVER
Acetaminophen
DYE-FREE
NO ARTIFICIAL FLAVORS
NO ALCOHOL, SACCHARIN OR DYES
GLUTEN FREE!
Natural BERRY Flavor
SEE NEW DOSING INFORMATION.
2 FL. OZ. (59 mL)